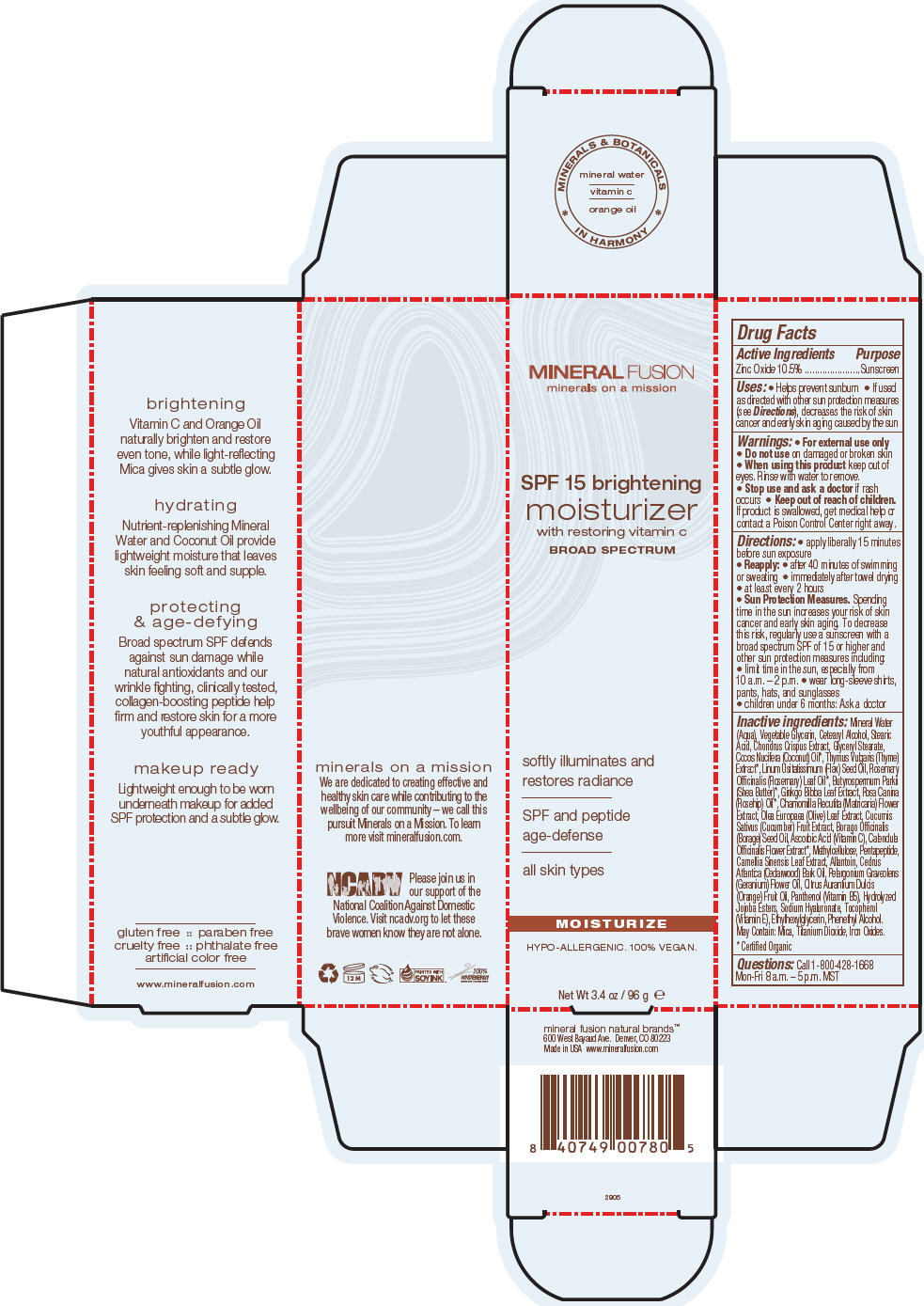 DRUG LABEL: SPF 15 BRIGHTENING MOISTURIZER
NDC: 55789-2905 | Form: CREAM
Manufacturer: Mineral Fusion Natural Brands
Category: otc | Type: HUMAN OTC DRUG LABEL
Date: 20150821

ACTIVE INGREDIENTS: ZINC OXIDE 10.8 g/96 g
INACTIVE INGREDIENTS: WATER 67.2 g/96 g; CETOSTEARYL ALCOHOL; STEARIC ACID; CHONDRUS CRISPUS CARRAGEENAN; GLYCERYL MONOSTEARATE; COCONUT OIL; THYME; LINSEED OIL; ROSEMARY OIL; SHEA BUTTER; GINKGO; ROSA CANINA FLOWER OIL; CHAMOMILE; OLEA EUROPAEA LEAF; CUCUMBER; BORAGE OIL; ASCORBIC ACID; CALENDULA OFFICINALIS FLOWER; METHYLCELLULOSE (400 MPA.S); GREEN TEA LEAF; ALLANTOIN; CEDRUS ATLANTICA BARK OIL; PELARGONIUM GRAVEOLENS FLOWER OIL; ORANGE; PANTHENOL; HYDROLYZED JOJOBA ESTERS (ACID FORM); HYALURONATE SODIUM; TOCOPHEROL; ETHYLHEXYLGLYCERIN; PHENYLETHYL ALCOHOL

SPF 15 BRIGHTENING MOISTURIZER

Drug Facts

Active Ingredients

Zinc Oxide 10.5%

Purpose

Sunscreen

Uses

- Helps prevent sunburn
- If used as directed with other sun protection measures (see Directions), decreases the risk of skin cancer and early skin aging caused by the sun

Warnings

- For external use only

- Do not use on damaged or broken skin

- When using this product keep out of eyes. Rinse with water to remove.

- Stop use and ask a doctor if rash occurs

- Keep out of reach of children. If product is swallowed, get medical help or contact a Poison Control Center right away.

Directions

- apply liberally 15 minutes before sun exposure
- Reapply:
  - after 40 minutes of swimming or sweating
  - immediately after towel drying
  - at least every 2 hours
- Sun Protection Measures. Spending time in the sun increases your risk of skin cancer and early skin aging. To decrease this risk, regularly use a sunscreen with a broad spectrum SPF of 15 or higher and other sun protection measures including:
  - limit time in the sun, especially from 10 a.m. – 2 p.m.
  - wear long-sleeve shirts, pants, hats, and sunglasses
- children under 6 months: Ask a doctor

Inactive ingredients

Mineral Water (Aqua), Vegetable Glycerin, Cetearyl Alcohol, Stearic Acid, Chondrus Crispus Extract, Glyceryl Stearate, Cocos Nucifera (Coconut) Oil [Certified Organic] , Thymus Vulgaris (Thyme) Extract, Linum Usitatissimum (Flax) Seed Oil, Rosemary Officinalis (Rosemary) Leaf Oil, Butyrospermum Parkii (Shea Butter), Ginkgo Biloba Leaf Extract, Rosa Canina (Rosehip) Oil, Chamomilla Recutita (Matricaria) Flower Extract, Olea Europaea (Olive) Leaf Extract, Cucumis Sativus (Cucumber) Fruit Extract, Borago Officinalis (Borage) Seed Oil, Ascorbic Acid (Vitamin C), Calendula Officinalis Flower Extract, Methylcellulose, Pentapeptide, Camellia Sinensis Leaf Extract, Allantoin, Cedrus Atlantica (Cedarwood) Bark Oil, Pelargonium Graveolens (Geranium) Flower Oil, Citrus Aurantium Dulcis (Orange) Fruit Oil, Panthenol (Vitamin B5), Hydrolyzed Jojoba Esters, Sodium Hyaluronate, Tocopherol (Vitamin E), Ethylhexylglycerin, Phenethyl Alcohol.
May Contain: Mica, Titanium Dioxide, Iron Oxides.

Questions

Call 1-800-428-1668

Mon-Fri 8 a.m. – 5 p.m. MST

PRINCIPAL DISPLAY PANEL - 96 g Tube Carton

MINERAL FUSION
minerals on a mission

SPF 15 brightening
moisturizer
with restoring vitamin c
BROAD SPECTRUM

softly illuminates and
restores radiance

SPF and peptide
age-defense

all skin types

MOISTURIZE
HYPO-ALLERGENIC. 100% VEGAN.

Net Wt 3.4 oz / 96 g e